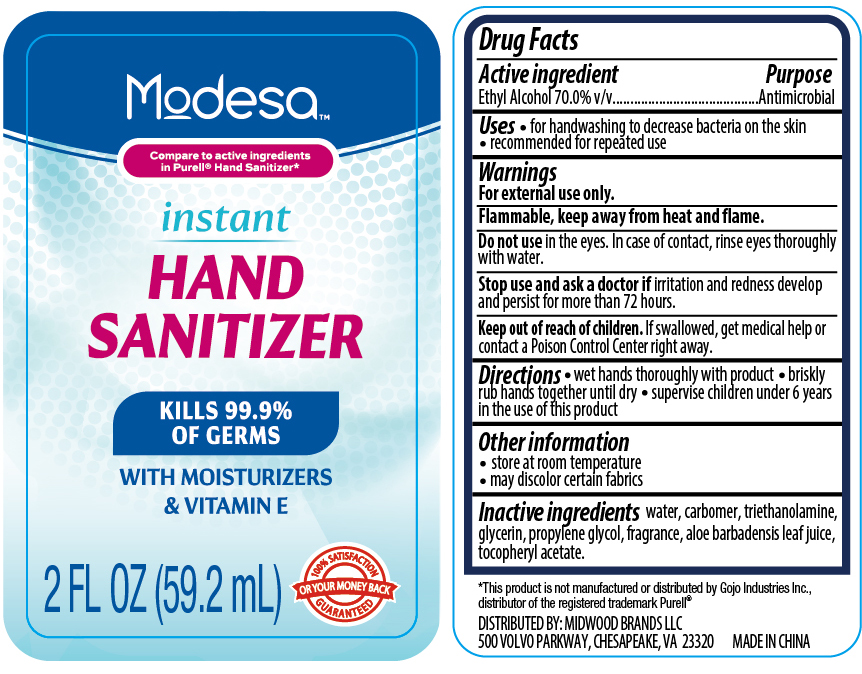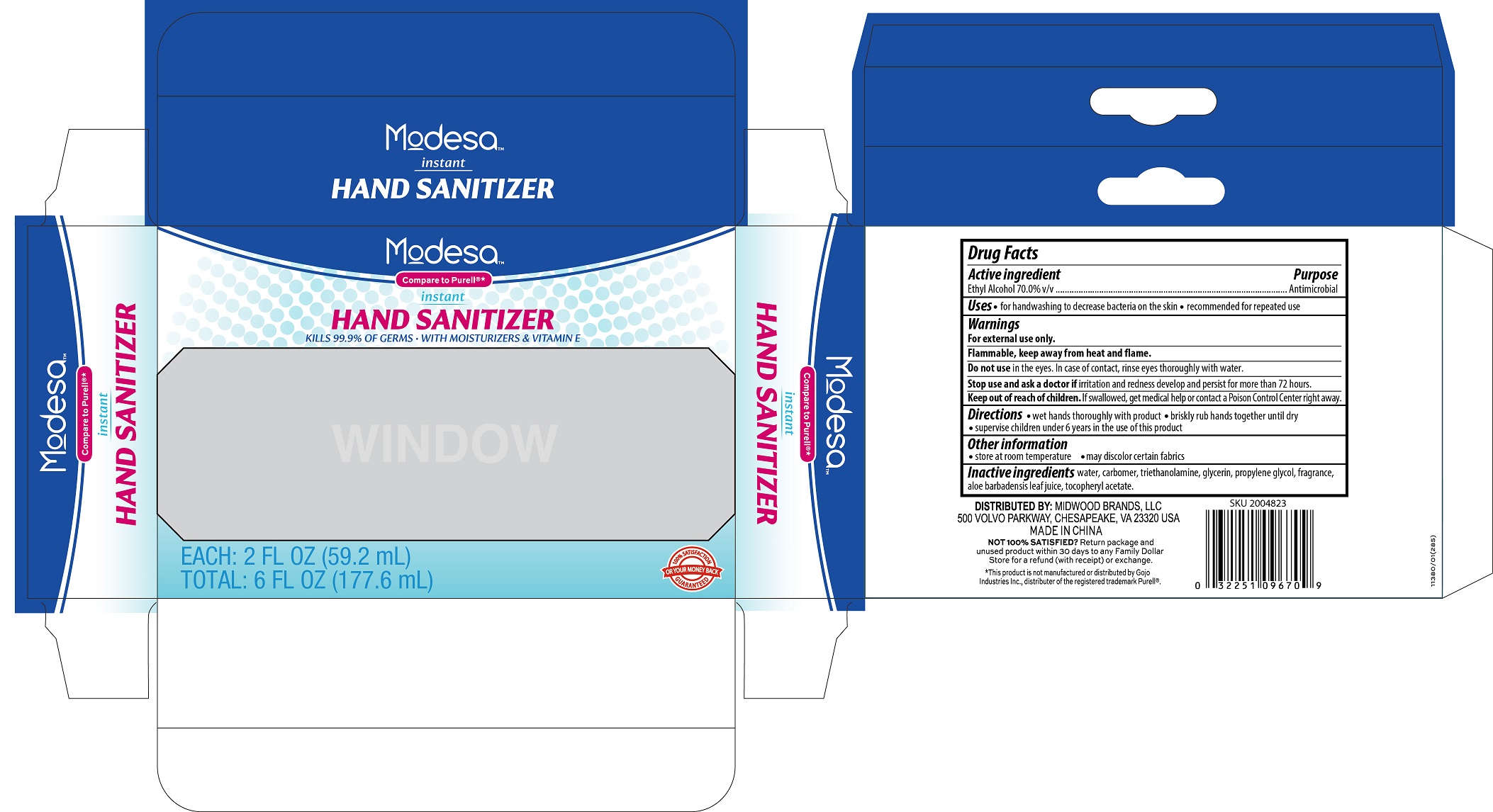 DRUG LABEL: Modesa Hand Sanitizer 2 fl.oz.
NDC: 58503-120 | Form: LIQUID
Manufacturer: China Ningbo Shangge Technology Co., Ltd.
Category: otc | Type: HUMAN OTC DRUG LABEL
Date: 20190626

ACTIVE INGREDIENTS: ALCOHOL 70 mL/100 mL
INACTIVE INGREDIENTS: WATER; CARBOMER 934; TROLAMINE; GLYCERIN; PROPYLENE GLYCOL; ALOE VERA LEAF; ALPHA-TOCOPHEROL ACETATE

Modesa Hand Sanitzer 2 fl. oz (3pk)

Active ingredient

Ethyl Alcohol 70.0% v/v

Purpose

Antimicrobial

Uses

- For handwashing to decrease bacteria on the skin
- Recommended for repeated use

Warnings

For external use only

Flammable, keep away from heat and flame.

Do not use in the eyes. In case of contact, rinse eyes thoroughly with water.

Stop use and ask a doctor if irritation and redness develop and persist for more than 72 hours.

Keep out of reach of children. If swallowed, get medical help or contact a Poison Control Center right away.

Directions

- Wet hands thoroughly with product
- Briskly rub hands together until dry
- Supervise children under 6 years in the use of this prodyuct

Other information

- Store at room temperature
- May discolor certain fabrics

Inactive ingredients

water, carbomer, triethanolamine, glycerin, propylene glycol, fragrance, aloe barbadensis leaf juice, tocopheryl acetate